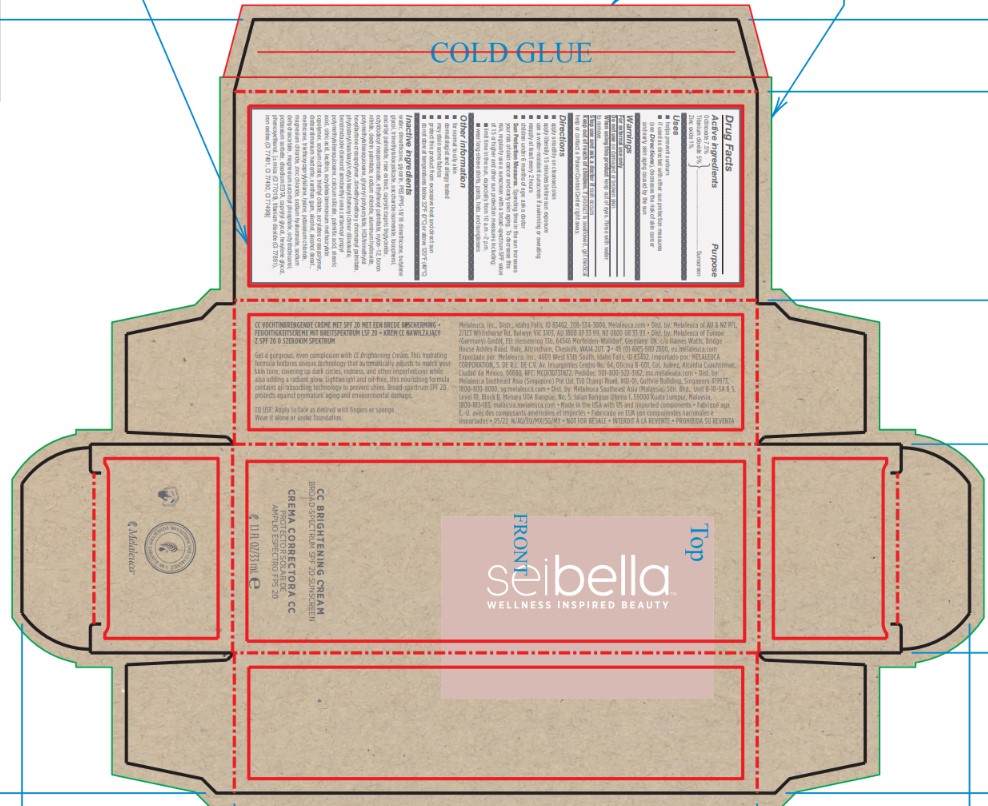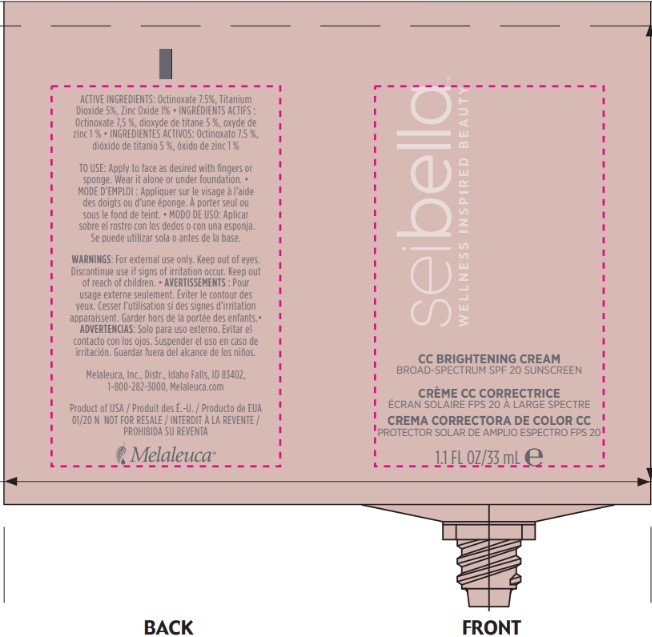 DRUG LABEL: Sei Bella CC Brightening Creme
NDC: 54473-282 | Form: LOTION
Manufacturer: Melaleuca Inc.
Category: otc | Type: HUMAN OTC DRUG LABEL
Date: 20251231

ACTIVE INGREDIENTS: TITANIUM DIOXIDE 1.65 g/33 mL; OCTINOXATE 2.475 g/33 mL; ZINC OXIDE 0.3267 g/33 mL
INACTIVE INGREDIENTS: ROSA CENTIFOLIA FLOWER OIL; WATER; NYLON-12; HEXAMETHYLENE DIISOCYANATE/TRIMETHYLOL HEXYLLACTONE CROSSPOLYMER; DIMETHYLMETHOXY CHROMANYL PALMITATE; CALCIUM SILICATE; CITRIC ACID MONOHYDRATE; AMMONIUM METHACRYLATE; TRIETHOXYCAPRYLYLSILANE; MAGNESIUM CHLORIDE; POTASSIUM SORBATE; POLYMETHYLSILSESQUIOXANE (4.5 MICRONS); DIMETHICONE; ETHYLHEXYL PALMITATE; SODIUM CHLORIDE; LECITHIN, SOYBEAN; XANTHAN GUM; OCTYLDODECANOL; BORON NITRIDE; SODIUM DEHYDROACETATE; PHENOXYETHANOL; PEG/PPG-18/18 DIMETHICONE; TRIMETHYLSILOXYSILICATE (M/Q 0.6-0.8); OCTYLDODECYL NEOPENTANOATE; SODIUM CITRATE; PHYTOSTERYL/ISOSTEARYL/CETYL/STEARYL/BEHENYL DIMER DILINOLEATE; PALMITIC ACID; STEARIC ACID; TRIETHYL CITRATE; DISTEARDIMONIUM HECTORITE; ALCOHOL; METHICONE (20 CST); MAGNESIUM ASCORBYL PHOSPHATE; CAPRYLYL GLYCOL; HEXYLENE GLYCOL; SACCHARIDE ISOMERATE; TOCOPHEROL; ASCORBYL PALMITATE; CAPRYLIC/CAPRIC/LINOLEIC TRIGLYCERIDE; ALUMINUM HYDROXIDE; BENZIMIDAZOLE; GLYCERIN; BUTYLENE GLYCOL; DEXTRIN PALMITATE (CORN; 20000 MW); POTASSIUM CHLORIDE; ZINC CHLORIDE

Sei Bella CC Brightening Creme - Medium Tan

Active Ingredient

Octinoxate 7.5%

Titanium Dioxide 5%

Zinc Oxide 1%

Purpose

Sunscreen

Use

- helps prevent sunburn
- if used as directed with other sun protection measures (see Directions), descreases the risk of skin cancer and early skin aging caused by the sun.

Warnings

For external use only

Do not use on damaged or broken skin

When using this product keep out of eyes. Rinse with water to remove.

Stop use and ask a doctor if rash occurs

Keep out of reach of children.

If product is swallowed, get medical help or contact a Poison Control Center right away.

Directions

■ apply smoothly on cleansed skin

■ apply liberally 15 minutes before sun exposure

■ use a water-resistant sunscreen if swimming or sweating

■ reapply at least every 2 hours

■ children under 6 months: ask a doctor

■ Sun Protection Measures. Spending time in the sun increases you risk of skin cancer and early skin aging. To decrease this risk, regularly use a sunscreen with a broad-spectrum SPF value of 15 or higher and other sun protection measures including:

■ limit time in the sun, especially from 10 a.m.-2 p.m.

■ wear long-sleeve shirts, pants, hats, and sunglasses

Other information

■ for normal to oily skin

■ dermatologist and allergy tested

STORAGE AND HANDLING

■ protect this product from excesssive heat and direct sun

■ do not store at temperatures below 32°F (0°C) or above 120°F (49°C)

Inactive ingredients

Aqua/Water/Eau, Dimethicone, Glycerin, PEG/PPG-18/18 Dimethicone, Butylene Glycol, Trimethylsiloxysilicate, Saccharide Isomerate, Tocopherol, Ascorbyl Palmitate, Rose Extract, Caprylic/Capric Triglyceride, Octyldodecyl Neopentanoate , Ethylhexyl Palmitate, Nylon-12, Boron Nitride, Dextrin Palmitate, Sodium Chloride, Aluminum Hydroxide, Polymethylsilsesquioxane, Glyceryl Polyacrylate, HDI/Trimethylol Hexyllactone Crosspolymer, Dimethylmethoxy Chromanyl Palmitate, Phytosteryl/Isostearyl/Cetyl/Stearyl/Behenyl Dimer Dilinoleate, Benzimidazole Diamond Amidoethyl Urea Carbamoyl Propyl Polymethylsilsesquioxane, Calcium Silicate, Palmitic Acid, Stearic Acid, Citric Acid , Lecithin, Acrylates/Ammonium Methacrylate Copolymer, Sodium Citrate, Triethyl Citrate , Acrylates Crosspolymer, Disteardimonium Hectorite, Xanthan Gum, Alcohol, Alcohol Denat., Methicone, Triethoxycaprylylsilane, Lysine, Potassium Chloride, Magnesium Chloride, Zinc Chloride, Sodium Hyaluronate, Sodium Dehydroacetate, Magnesium Ascorbyl Phosphate, Octyldodecanol, Potassium Sorbate, Disodium EDTA, Caprylyl Glycol, Hexylene Glycol, Phenoxyethanol

May Contain (+/-)
Mica, Titanium Dioxide (CI 77891), Iron Oxides (CI 77491, CI 77492, CI 77499)